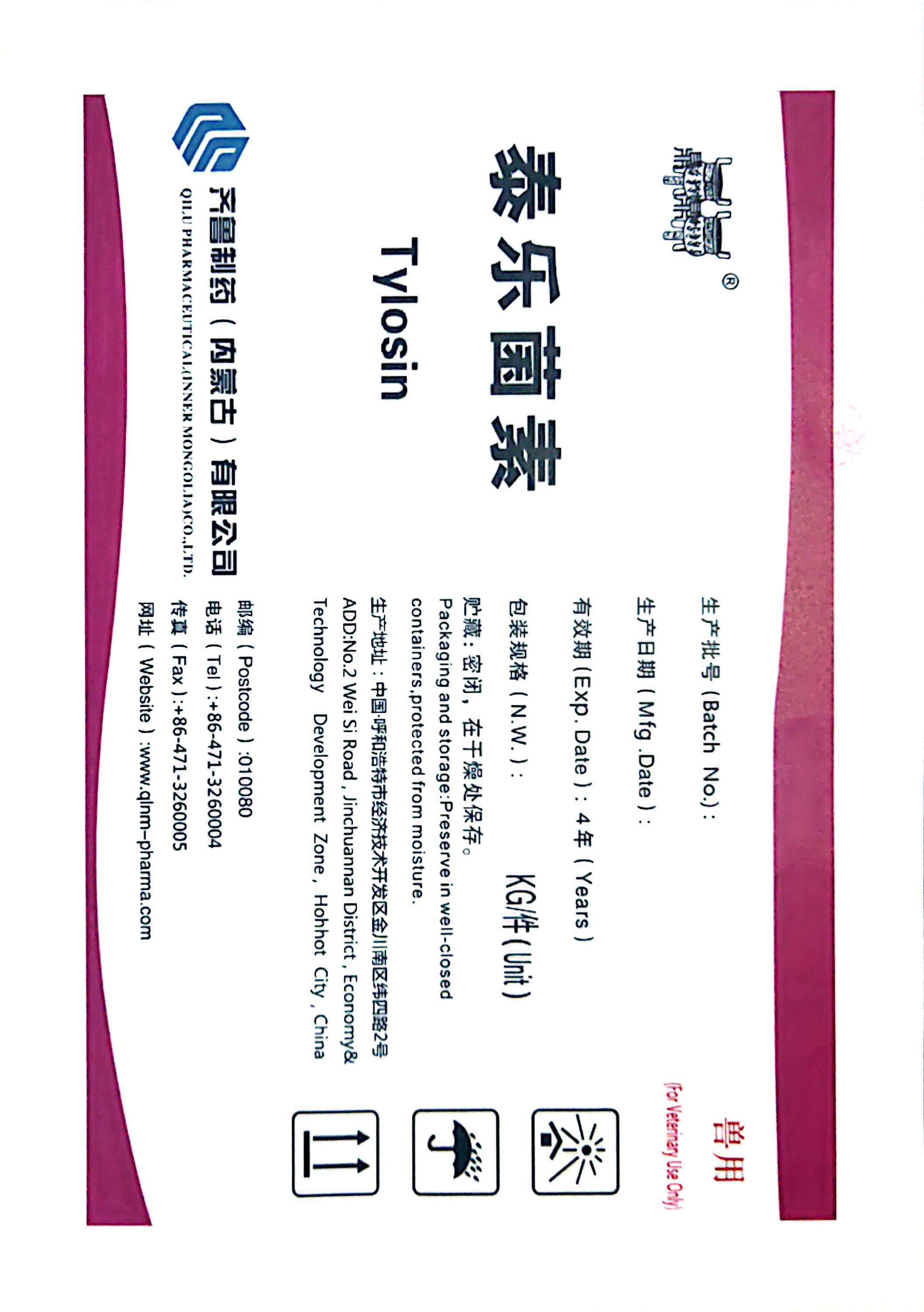 DRUG LABEL: Tylosin
NDC: 86098-0002 | Form: POWDER
Manufacturer: Qilu Pharmaceutical (Inner Mongolia) Co., Ltd.
Category: other | Type: BULK INGREDIENT - ANIMAL DRUG
Date: 20251120

ACTIVE INGREDIENTS: TYLOSIN 15 kg/15 kg

Tylosin

PACKAGE LABEL

Tylosin
QILU PHARMACEUTICAL (INNER MONGOLIA) CO.,LTD.
ADD:No.2 Wei Si Road, Jinchuannan District, Economy &Technology Development Zone, Hohhot City, China
Batch No.:
Mfg.Date:
Exp.Date: 4 Years
N.W.: KG/Unit
Packaging and storage: Preserve in well-closed containers, protected from moisture.
Postcode:010080
Tel:+86-471-3260004
Fax:+86-471-3260005
Website: www.qlnm-pharma.com